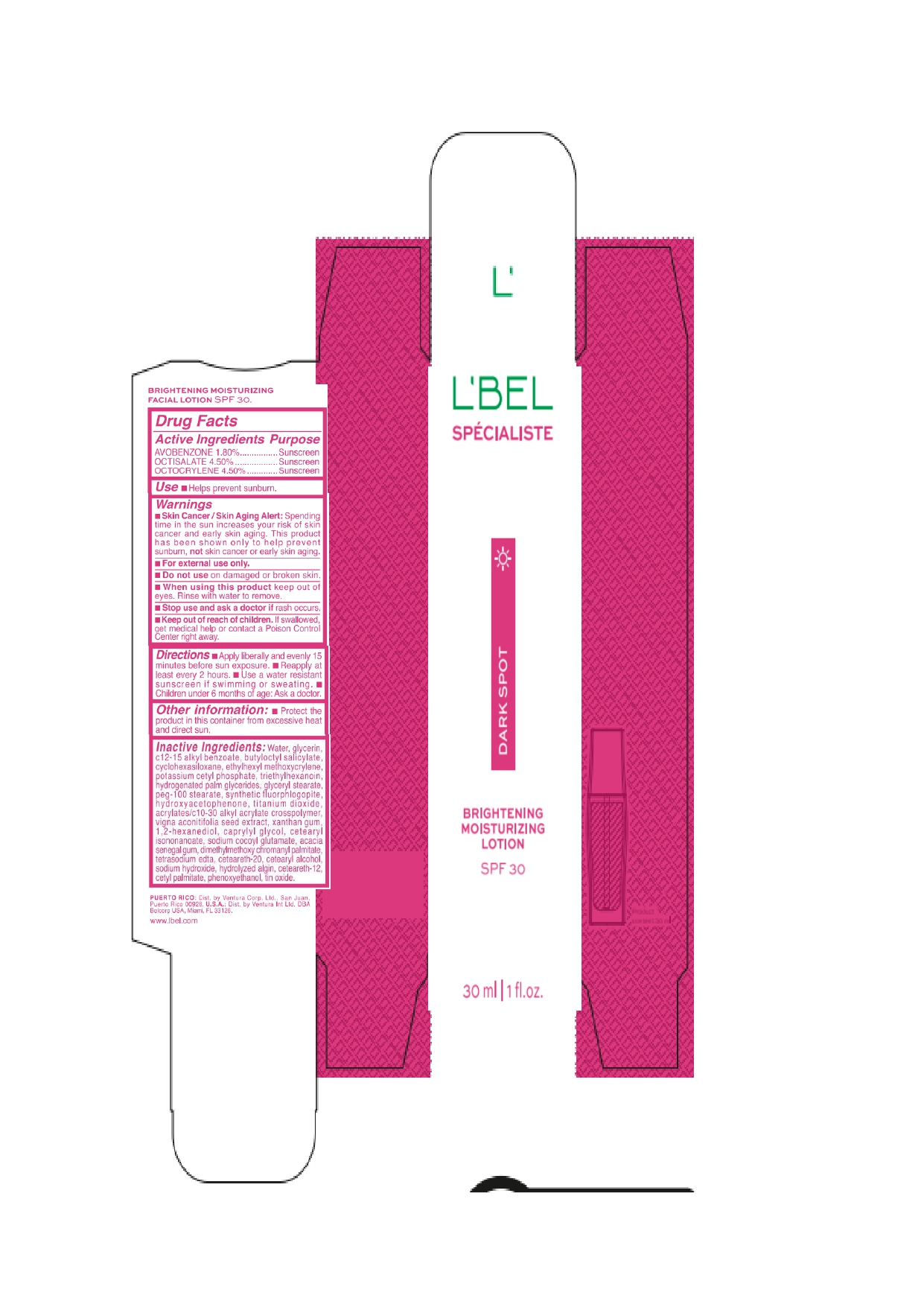 DRUG LABEL: LBEL SPECIALISTE DARK SPOT BRIGHTENING MOISTURIZING SPF 30
NDC: 14141-332 | Form: EMULSION
Manufacturer: BEL STAR SA
Category: otc | Type: HUMAN OTC DRUG LABEL
Date: 20241028

ACTIVE INGREDIENTS: AVOBENZONE 18 mg/1 mL; OCTISALATE 45 mg/1 mL; OCTOCRYLENE 45 mg/1 mL
INACTIVE INGREDIENTS: CARBOMER COPOLYMER TYPE B (ALLYL PENTAERYTHRITOL CROSSLINKED); WATER; BUTYLOCTYL SALICYLATE; ETHYLHEXYL METHOXYCRYLENE; MOTH BEAN; CYCLOMETHICONE 5; POTASSIUM CETYL PHOSPHATE; STANNOUS OXIDE; ALKYL (C12-15) BENZOATE; TITANIUM DIOXIDE; GELATIN HYDROLYSATE (PORCINE SKIN, MW 3000); PHENOXYETHANOL; MAGNESIUM POTASSIUM ALUMINOSILICATE FLUORIDE; TRIETHYLHEXANOIN; CETYL PALMITATE; HYDROGENATED PALM GLYCERIDES; GLYCERYL MONOSTEARATE; PEG-100 STEARATE; CETOSTEARYL ALCOHOL; GLYCERIN; XANTHAN GUM; HYDROXYACETOPHENONE; CAPRYLYL GLYCOL; EDETATE SODIUM; 1,2-HEXANEDIOL; ACACIA; CETEARYL ISONONANOATE; SODIUM COCOYL GLUTAMATE; POLYOXYL 20 CETOSTEARYL ETHER; CETEARETH-12; DIMETHYLMETHOXY CHROMANYL PALMITATE; SODIUM HYDROXIDE

LBEL SPECIALISTE DARK SPOT BRIGHTENING MOISTURIZING SPF 30

Active Ingredients

Avobenzone 1.80%

Octisalate 4.50%

Octocrylene 4.50%

Purpose

Sunscreen

Uses

- Helps prevent sunburn.

Warnings

- Skin Cancer / Skin Aging Alert: Spending time in the sun increases your risk of skin cancer and early skin aging. This product has been shown only to help prevent sunburn, not skin cancer or early skin aging.
- For external use only.

Do not use

on damaged or broken skin.

When using this product

keep out of eyes. Rinse with water to remove.

Stop use and ask a doctor if

rash occurs.

Keep out of reach of children.

If swallowed, get medical help or contact a Poison Control Center right away.

Directions

- Apply liberally and evenly 15 minutes before sun exposure.
- Reapply at least every 2 hours
- Use a water resistant sunscreen if swimming or sweating.
- Children under 6 months of age: Ask a doctor

Other information

Protect the product in this container from excessive heat and direct sun.

Inactive ingredients

Water, glycerin, c12-15 alkyl benzoate, butyloctyl salicylate, cyclohexasiloxane, ethylhexyl methoxycrylene, potassium cetyl phosphate, triethylhexanoin, hydrogenated palm glycerides, glyceryl stearate, peg-100 stearate, synthetic fluorphlogopite, hydroxyacetophenone, titanium dioxide, acrylates/c10-30 alkyl acrylate crosspolymer, vigna aconitifolia seed extract, xanthan gum, 1,2-hexanediol, caprylyl glycol, cetearyl isononanoate, sodium cocoyl glutamate, acacia senegal gum, dimethylmethoxy chromanyl palmitate, tetrasodium edta, ceteareth-20, cetearyl alcohol, sodium hydroxide, hydrolyzed algin, ceteareth-12, cetyl palmitate, phenoxyethanol, tin oxide.

Company Information

PUERTO RICO: Dist. by Ventura Corp, Ltd., San Juan, Puerto Rico 00926, U.S.A.: Dist. by Ventura Int Ltd. DBA Belcorp USA, Miami, FL 33126 .

www.lbel.com